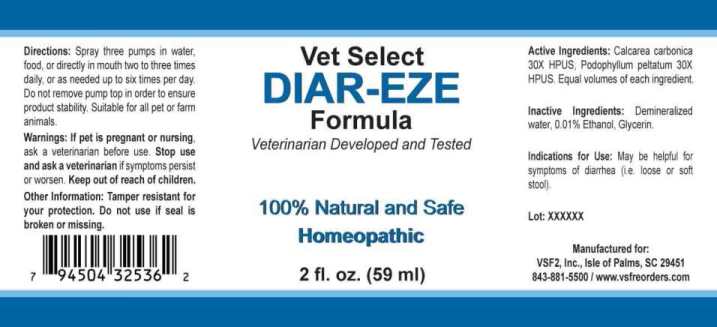 DRUG LABEL: Diar-Eze
NDC: 86100-0006 | Form: LIQUID
Manufacturer: Vsf2, Inc.
Category: homeopathic | Type: OTC ANIMAL DRUG LABEL
Date: 20251110

ACTIVE INGREDIENTS: OYSTER SHELL CALCIUM CARBONATE, CRUDE 30 [hp_X]/1 mL; PODOPHYLLUM 30 [hp_X]/1 mL
INACTIVE INGREDIENTS: WATER; ALCOHOL; GLYCERIN

Drug Facts:

ACTIVE INGREDIENTS:

Calcarea Carbonica 30X HPUS, Podophyllum Peltatum 30X HPUS.

INDICATIONS FOR USE:

May be helpful for symptoms of diarrhea (i.e. loose or soft stool).

WARNINGS:

If pet is pregnant or nursing, ask a veterinarian before use.

Stop use and ask a veterinarian if symptoms persist or worsen.

Keep out of reach of children.

Other Information: Tamper resistant for your protection. Do not use if seal is broken or missing.

KEEP OUT OF THE REACH OF CHILDREN:

Keep out of reach of children.

DIRECTIONS:

Spray three pumps in water, food or directly in mouth two to three times daily, or as needed up to six times per day. Do not remove pump top in order to ensure product stability. Suitable for all pet or farm animals.

INDICATIONS FOR USE:

May be helpful for symptoms of diarrhea (i.e. loose or soft stool).

INACTIVE INGREDIENTS:

Demineralized water, 0.01% Ethanol, Glycerin.

QUESTIONS:

Manufactured in the USA for:

VSF2, Inc., Isle of Palms, SC 29451

843-881-5500 / www.vsfreorders.com

PACKAGE LABEL DISPLAY:

Vet Select

DIAR-EZE

Formula

Veterinarian Developed and Tested

100% Natural and Safe

Homeopathic

2 fl. oz. (59 ml)